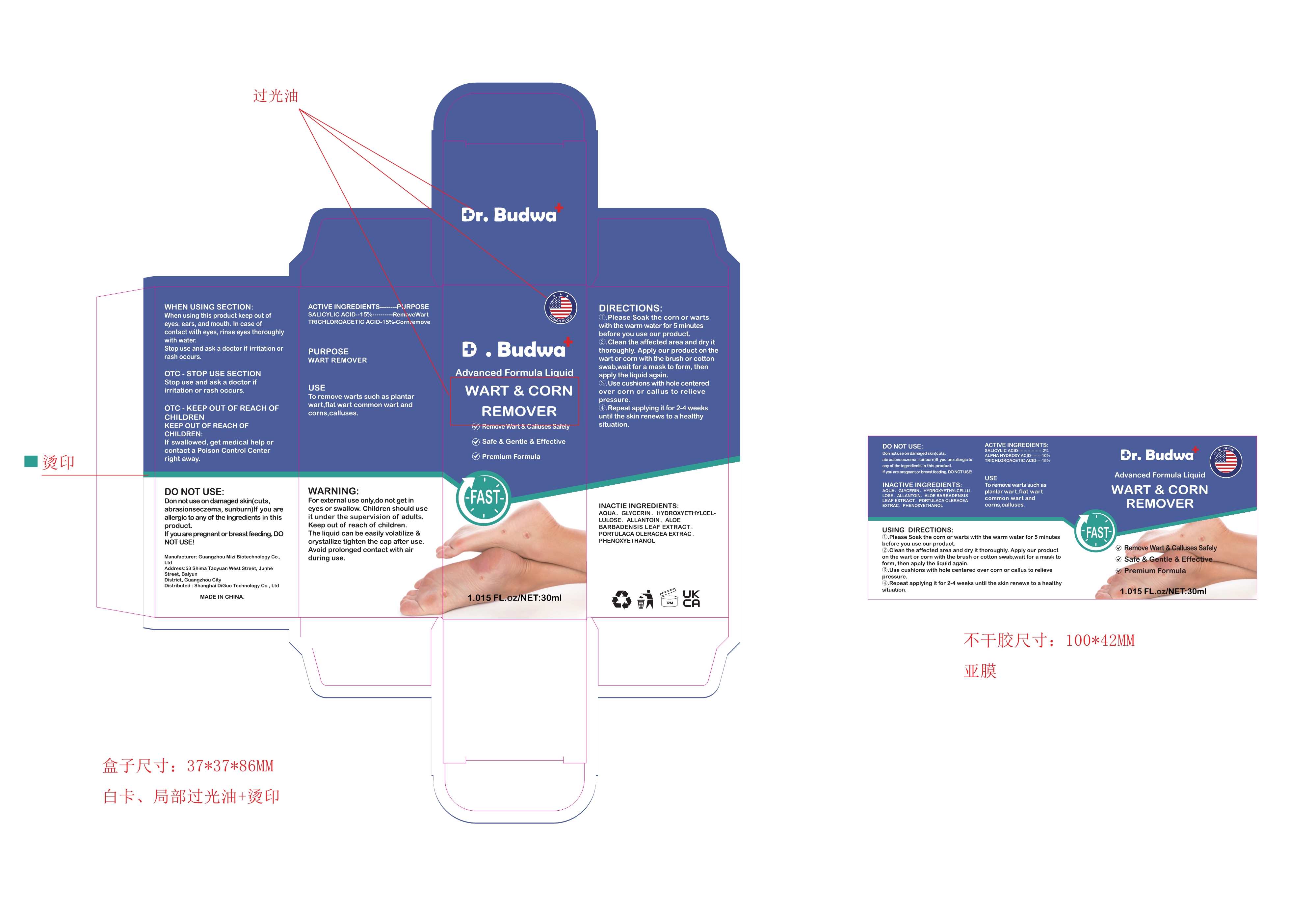 DRUG LABEL: Wart Remover Liquid
NDC: 84251-002 | Form: LIQUID
Manufacturer: Shanghai DiGuo Technology Co., Ltd
Category: otc | Type: HUMAN OTC DRUG LABEL
Date: 20240429

ACTIVE INGREDIENTS: TRICHLOROACETIC ACID 15 g/100 mL; SALICYLIC ACID 15 g/100 mL
INACTIVE INGREDIENTS: ALLANTOIN; PHENOXYETHANOL; GLYCERIN; ALOE VERA LEAF; WATER; PURSLANE; HYDROXYETHYL CELLULOSE, UNSPECIFIED

84251-002

Active Ingredient(s)

SALICYLIC ACID-2%

Alpha Hydroxy acid-10%

TRICHLOROACETIC ACID-15%

Purpose

WART REMOVER

Use

To remove warts such as plantar wart,flat wart common wart and corns,calluses.

Warnings

For extermal use only,do not get in eyes or swallow. Children should use it under the supervision of adults.

Keep out of reach of children. The liquid can be easily volatilize & crystallize tighten the cap after use. Awoid

prolonged contact with air during use.

Do not use

Donnotuse on da maged skin(cuts, abrasionseczema, sunburn)f you are
allergic to any of the ingredients in this product. If you are pregnantor breastfeeding,

DO NOTUSE!

When using this product keep out of eyes, ears, and mouth. In case of contact with eyes,

rinse eyes thoroughly with water. Stop use and ask a doctor if irritation or rash occurs.

Stop use and ask a doctor if irritation or rash occurs.

KEEP OUT OF REACH OF CHILDREN

If swallowed, get medical help or contact a Poison Control Center right away.

Directions

①.Please Soak the corn or warts with the warm water for 5 minutes before you use our product.
②.Clean the affected area and dry it thoroughly. Apply our product on the wart or corn with the brush or cotton
swab,wait for a mask to form, then apply the liquid again.
③.Use cushions with hole centered over corn or callus to relieve pressure.
④.Repeat applying it for 2-4 weeks until the skin renews to a healthy situation.

Other information

No data available

Inactive ingredients

AQUA、GLYCERIN、 HYDROXYETHYLCEL-LULOSE、

ALL ANTOIN、ALOE BARBADENSIS LEAF EXTRACT、

PORTUL ACA OL .ERACEA EXTRAC、PHENOXYETHANOL